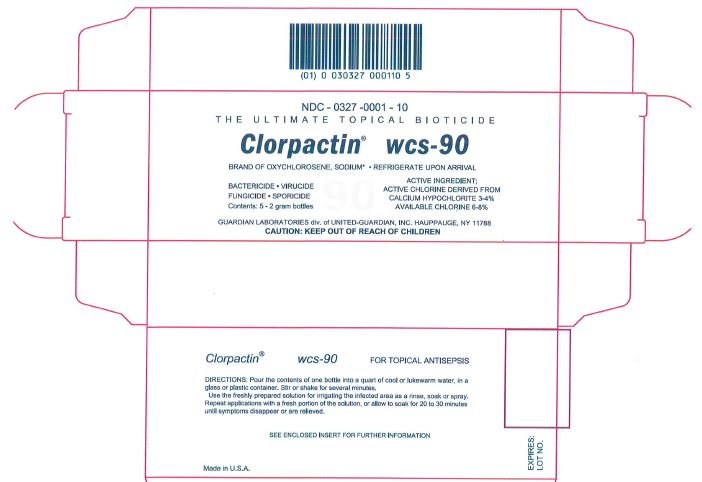 DRUG LABEL: Clorpactin WCS-90
NDC: 0327-0001 | Form: POWDER, FOR SOLUTION
Manufacturer: United-Guardian, Inc.
Category: otc | Type: HUMAN OTC DRUG LABEL
Date: 20221023

ACTIVE INGREDIENTS: CHLORINE 0.16 g/2 g
INACTIVE INGREDIENTS: SODIUM ACID PYROPHOSPHATE; SODIUM POLYMETAPHOSPHATE; SODIUM DODECYLBENZENESULFONATE

Clorpactin® WCS-90

Active ingredient

Active Chlorine Derived from Calcium Hypochlorite 3-4%
Available Chlorine 6-8%

Purpose

Topical Antisepsis

Uses

Topical Antisepsis

Warnings

Caution

Never use Clorpactin WCS-90 powder as is. This product is intended to be used only as a solution (in water). The powder can cause damage to human tissue, and particularly to infected areas or mucous membrane tissue.

Directions

Add the Clorpactin WCS-90 powder to sterile or deionized water at room temperature (20-25° C.). The powder dissolves slowly in water. As a result even after 2-3 minutes of stirring or mixing some residue of incompletely dissolved product will remain. This residue consists of inactive ingredients and therefore there is no necessity to continue to stir or mix for a longer period of time. This residue can be removed by either filtering the solution through a coarse laboratory filter or allowing the solution to settle for about 5 minutes and then decanting the clear solution for use.

Storage

Clorpactin WCS-90 solutions should preferably be used as soon as possible after preparation. If the solution must be stored, it can be kept refrigerated (2-8° C.) for up to 10 days in a capped or sealed plastic or glass container using a non-metallic cap. It can be stored at room temperature (20-25° C.) for up to 3 days after preparation.

Handling

As with any chlorinated product, Clorpactin WCS-90 solution should be prepared in a ventilated area and inhalation of the vapors should be minimized. The solution can cause bleaching of fabrics or other materials if splashing or spilling occurs.

Inactive ingredients

sodium acid pyrophosphate, sodium hexametaphosphate, sodium dodecylbenzene sulfonate

PW018 – Revised August 25, 2021

Package/Label Principal Display Panel

NDC - 0327 -0001 - 10

THE ULTIMATE TOPICAL BIOTICIDE

Clorpactin® wcs-90

BRAND OF OXYCHLOROSENE, SODIUM* • REFRIGERATE UPON ARRIVIAL

BACTERICIDE • VIRUCIDE
FUNGICIDE • SPORICIDE
Contents: 5 - 2 gram bottles

ACTIVE INGREDIENT:
ACTIVE CHLORINE DERIVED FROM
CALCIUM HYPOCHLORITE 3-4%
AVAILABLE CHLORINE 6-8%

GUARDIAN LABORATORIES div. of UNITED-GUARDIAN, INC. HAUPPAUGE, NY 11788
CAUTION: KEEP OUT OF REACH OF CHILDREN

Clorpactin® wcs-90 FOR TOPICAL ANTISEPSIS

DIRECTIONS: Pour the contents of one bottle into a quart of cool or lukewarm water, in a
glass or plastic container. Stir or shake for several minutes.
Use the freshly prepared solution for irrigating the infected area as a rinse, soak or spray.
Repeat applications with a fresh portion of the solution, or allow to soak for 20 to 30 minutes until symptoms disappear or are relieved.

SEE ENCLOSED INSERT FOR FURTHER INFORMATION

Made in U.S.A.

Box Label